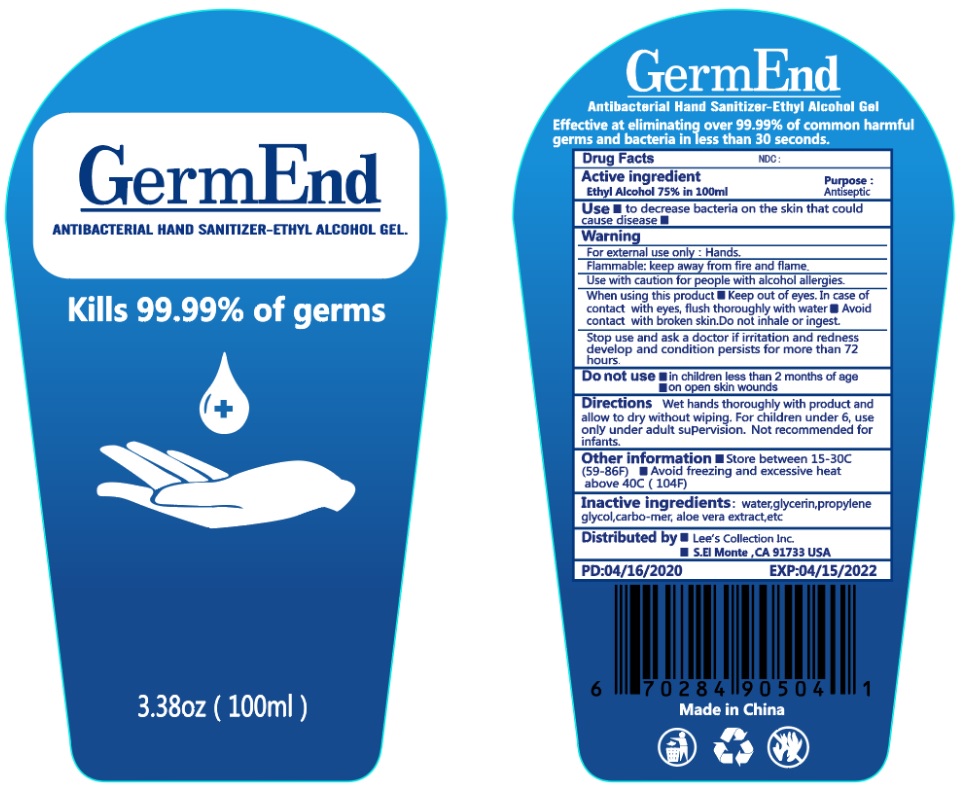 DRUG LABEL: Germ End Antibacterial Hand Sanitizer
NDC: 74027-200 | Form: GEL
Manufacturer: Lee's Collection Inc.
Category: otc | Type: HUMAN OTC DRUG LABEL
Date: 20200420

ACTIVE INGREDIENTS: ALCOHOL 75 mL/100 mL
INACTIVE INGREDIENTS: WATER; GLYCERIN; PROPYLENE GLYCOL; CARBOMER HOMOPOLYMER, UNSPECIFIED TYPE; ALOE VERA LEAF

GermEnd ANTIBACTERIAL HAND SANITIZER

Active ingredient

Ethyl alcohol 75%

Purpose :

Antiseptic

INDICATIONS AND USAGE

Use ▪ to decrease bacteria on the skin that could cause disease ▪

Warning

For external use only : Hands.

Flammable: keep away from fire and flame.

Use with caution for people with alcohol allergies.

When using this product ▪ Keep out of eyes. In case of contact with eyes, flush thoroughly with water ▪ Avoid contact with broken skin. Do not inhale or ingest.

Stop use and ask a doctor if irritation and redness develop and condition persists for more than 72 hours.

Keep out of reach of children.

DOSAGE AND ADMINISTRATION

Directions Wet hands thoroughly with product and allow to dry without wiping. For children under 6, use only under adult supervision. Not recommended for infants.

Other information ▪ Store between 15-30C (59-86F) ▪ Avoid freezing and excessive heat above 40C (104F)

INACTIVE INGREDIENT

Inactive ingredients: water, glycerin, propylene glycol, carbo-mer, aloe vera extract, etc

Kills 99.99% of germs

Effective at eliminating over 99.99% of common harmful germs and bacteria in less than 30 seconds.

Distributed by ▪ Lee's Collection Inc.

S.EI Monte ,CA 91733

PD:04/16/2020

EXP:04/15/2022

Made in China